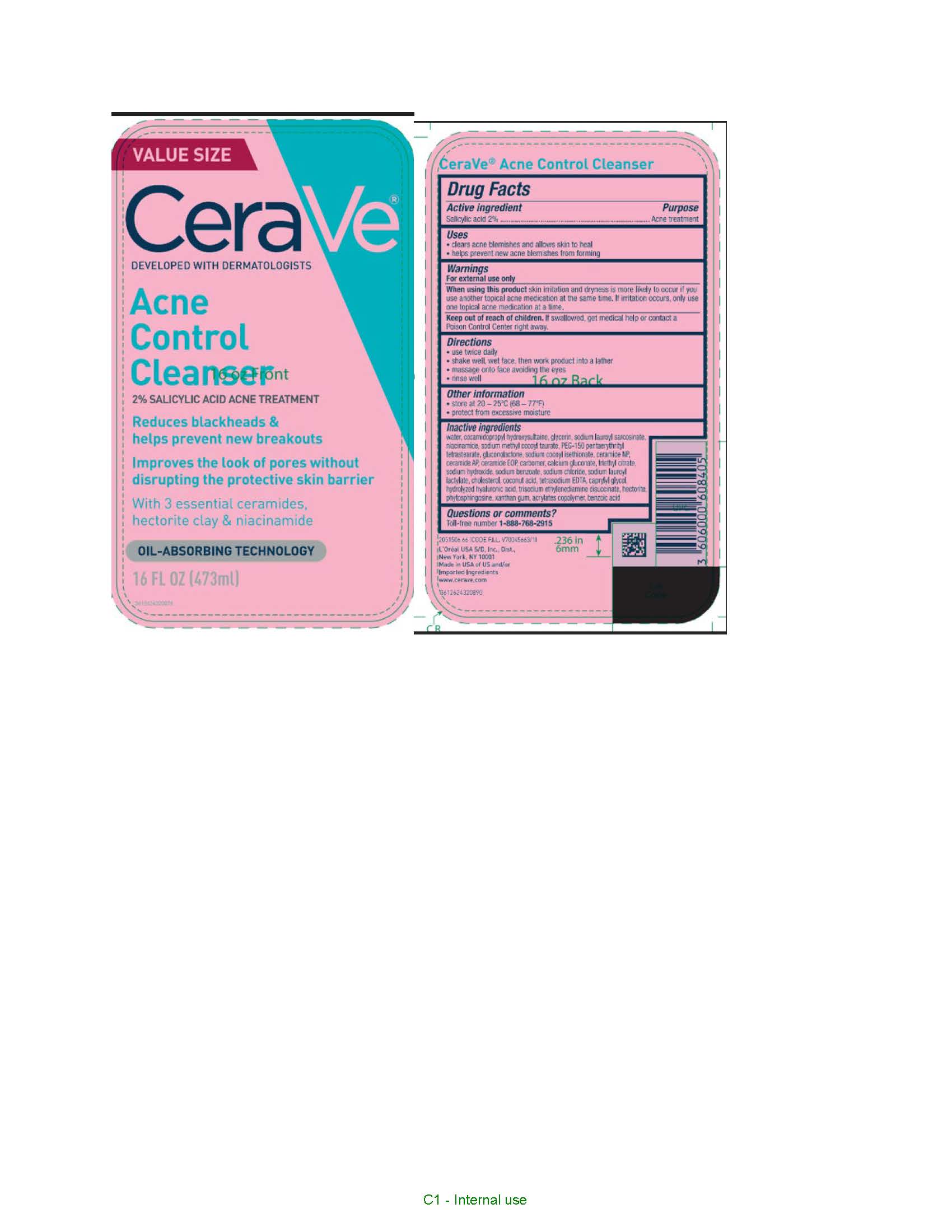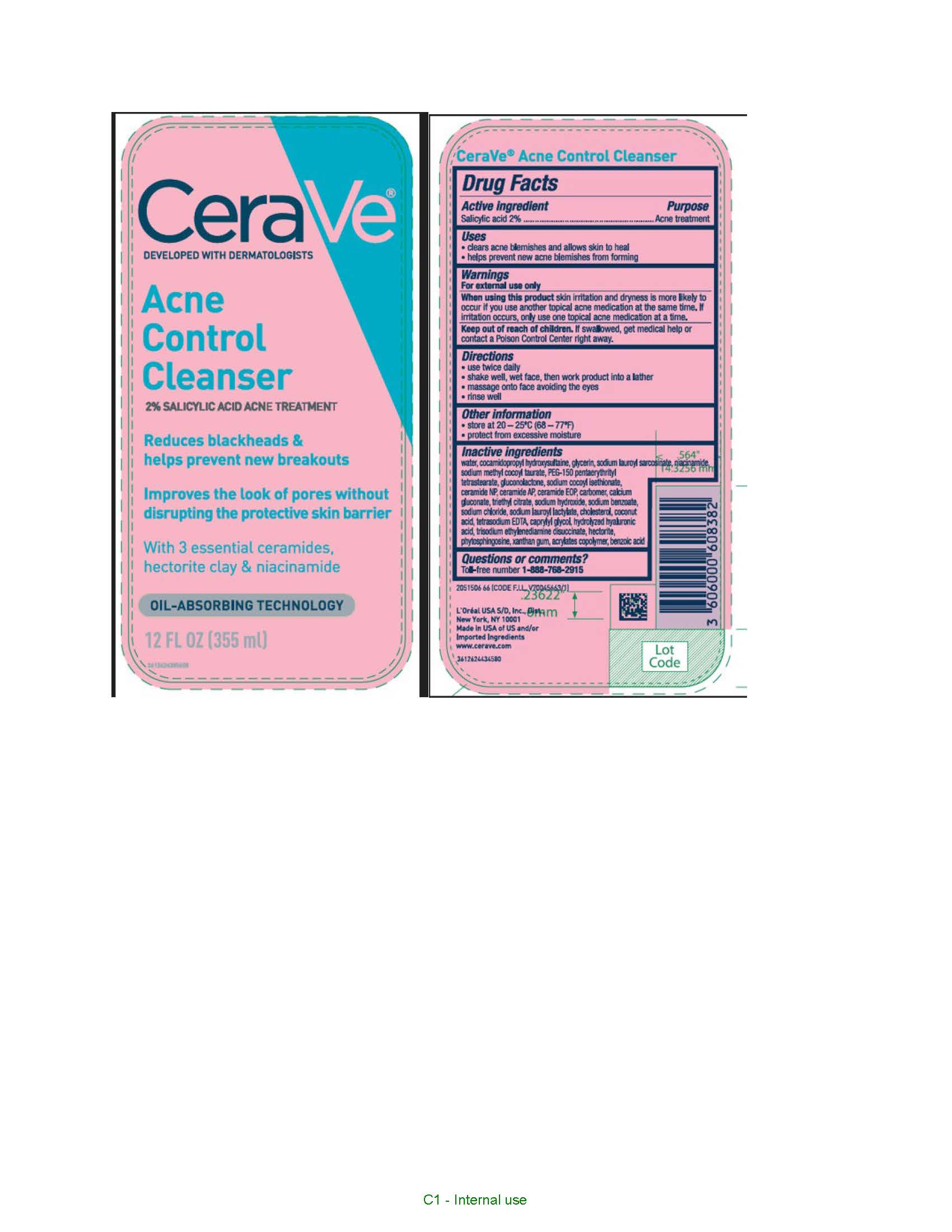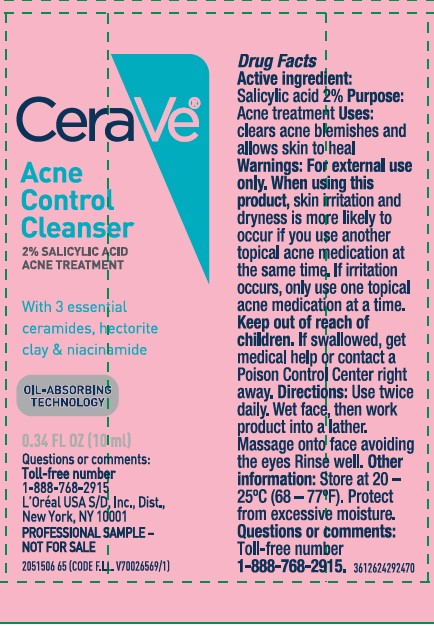 DRUG LABEL: CeraVe Developed with Dermatologists Acne Control Cleanser Oil Absorbing Technology
NDC: 49967-840 | Form: GEL
Manufacturer: L'Oreal USA Products Inc
Category: otc | Type: HUMAN OTC DRUG LABEL
Date: 20250328

ACTIVE INGREDIENTS: Salicylic Acid 20 mg/1 mL
INACTIVE INGREDIENTS: WATER; SODIUM LAUROYL SARCOSINATE; COCAMIDOPROPYL HYDROXYSULTAINE; GLYCERIN; NIACINAMIDE; GLUCONOLACTONE; SODIUM COCOYL ISETHIONATE; SODIUM METHYL COCOYL TAURATE; PEG-150 PENTAERYTHRITYL TETRASTEARATE; XANTHAN GUM; SODIUM BENZOATE; SODIUM CHLORIDE; SODIUM HYDROXIDE; HECTORITE; TRISODIUM ETHYLENEDIAMINE DISUCCINATE; SODIUM LAUROYL LACTYLATE; CHOLESTEROL; COCONUT ACID; EDETATE SODIUM; CALCIUM GLUCONATE; CERAMIDE NP; TRIETHYL CITRATE; CAPRYLYL GLYCOL; CERAMIDE AP; PHYTOSPHINGOSINE; HYALURONIC ACID; CARBOMER HOMOPOLYMER, UNSPECIFIED TYPE; BENZOIC ACID; CERAMIDE 1

Drug Facts

Active ingredient

Salicylic acid 2%

Purpose

Acne treatment

Uses

- clears acne blemishes and allows skin to heal
- helps prevent new acne blemishes from forming

Warnings

For external use only

When using this product

skin irritation and dryness is more likely to occur if you use another topical acne medication at the same time. if irritation occurs, only use one topical acne medication at a time.

Keep out of reach of children.

If swallowed, get medical help or contact a Poison Control Center right away.

Directions

- use twice daily
- shake well, wet face, then work product into a lather
- massage onto face avoiding the eyes
- rinse well

Inactive ingredients

water, cocamidopropyl hydroxysultaine, glycerin, sodium lauroyl sarcosinate, niacinamide, sodium methyl cocoyl taurate, PEG-150 pentaerythrityl tetrastearate, gluconolactone, sodium cocoyl isethionate, ceramide NP, ceramide AP, ceramide EOP, carbomer, calcium gluconate, triethyl citrate, sodium hydroxide, sodium benzoate, sodium chloride, sodium lauroyl lactylate, cholesterol, coconut acid, tetrasodium EDTA, caprylyl glycol, hydrolyzed hyaluronic acid, trisodium ethylenediamine disuccinate, hectorite, phytosphingosine, xanthan gum, acrylates copolymer, benzoic acid